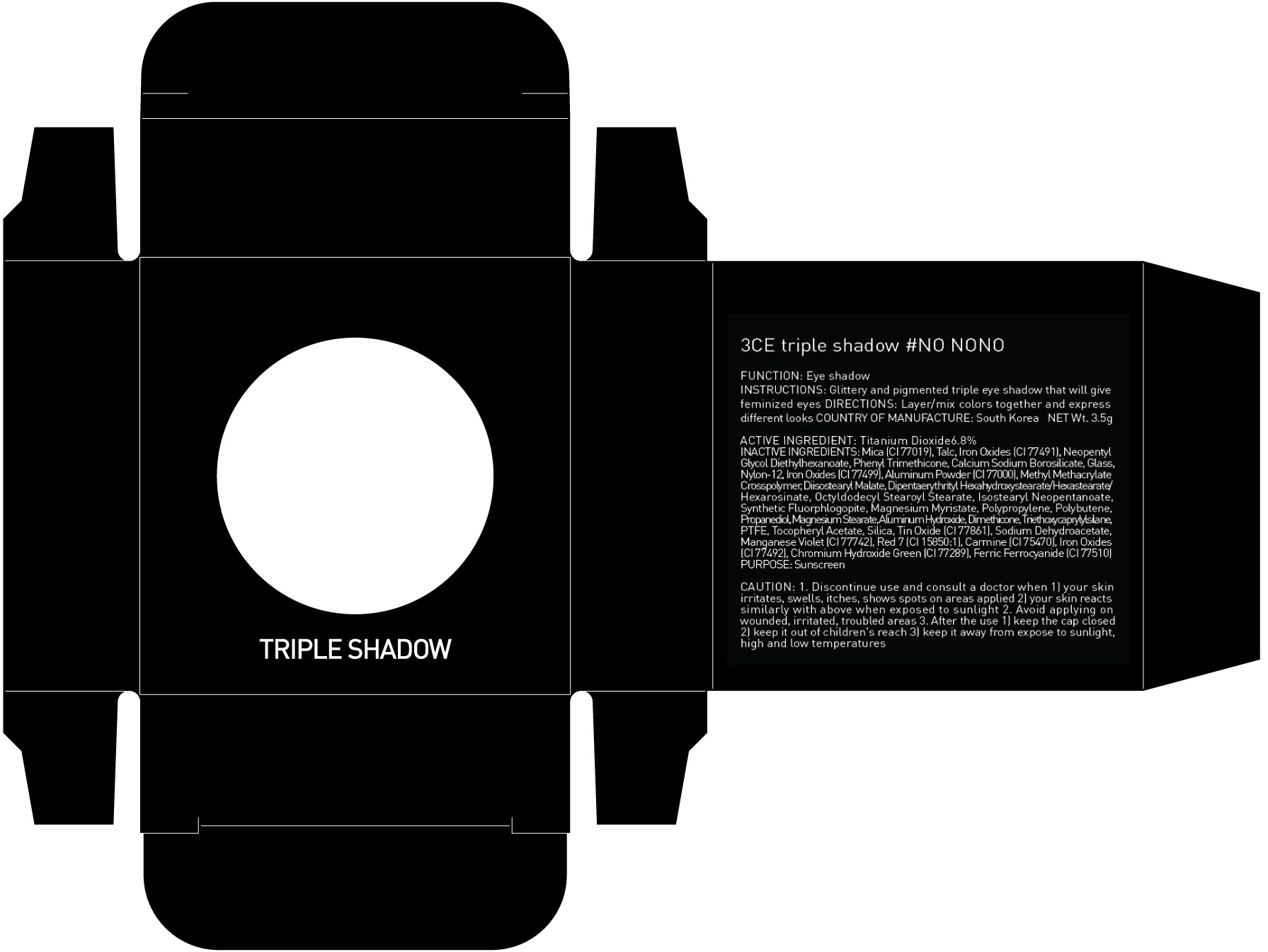 DRUG LABEL: 3CE TRIPLE SHADOW NO NONO
NDC: 60764-025 | Form: POWDER
Manufacturer: Nanda Co., Ltd
Category: otc | Type: HUMAN OTC DRUG LABEL
Date: 20160922

ACTIVE INGREDIENTS: Titanium Dioxide 0.23 g/3.5 g
INACTIVE INGREDIENTS: Mica; Talc

ACTIVE INGREDIENT

Active Ingredient: Titanium Dioxide 6.8%

INACTIVE INGREDIENT

Inactive Ingredients: Mica (CI 77019), Talc, Iron Oxides (CI 77491), Neopentyl Glycol Diethylhexanoate, Phenyl Trimethicone, Calcium Sodium Borosilicate, Glass, Nylon-12, Iron Oxides (CI 77499), Aluminum Powder (CI 77000), Methyl Methacrylate Crosspolymer, Diisostearyl Malate, Dipentaerythrityl Hexahydroxystearate/Hexastearate/Hexarosinate, Octyldodecyl Stearoyl Stearate, Isostearyl Neopentanoate, Synthetic Fluorphlogopite, Magnesium Myristate, Polypropylene, Polybutene, Propanediol, Magnesium Stearate, Aluminum Hydroxide, Dimethicone, Triethoxycaprylylsilane, PTFE, Tocopheryl Acetate, Silica, Tin Oxide (CI 77861), Sodium Dehydroacetate, Manganese Violet (CI 77742), Red 7 (CI 15850:1), Carmine (CI 75470), Iron Oxides (CI 77492), Chromium Hydroxide Green (CI 77289), Ferric Ferrocyanide (CI 77510)

PURPOSE

Purpose: Sunscreen

CAUTION

CAUTION: 1. Discontinue use and consult a doctor when - your skin irritates, swells, itches, shows spots on areas applied - your skin reacts similarly with above when exposed to sunlight 2. Avoid applying on wounded, irritated, troubled areas 3. After the use - keep the cap closed - keep it out of children's reach - keep it away from expose to sunlight, high and low temperatures

DESCRIPTION

INSTRUCTIONS: Glittery and pigmented triple eye shadow that will give feminized eyes.

Directions: Layer/mix colors together and express different looks